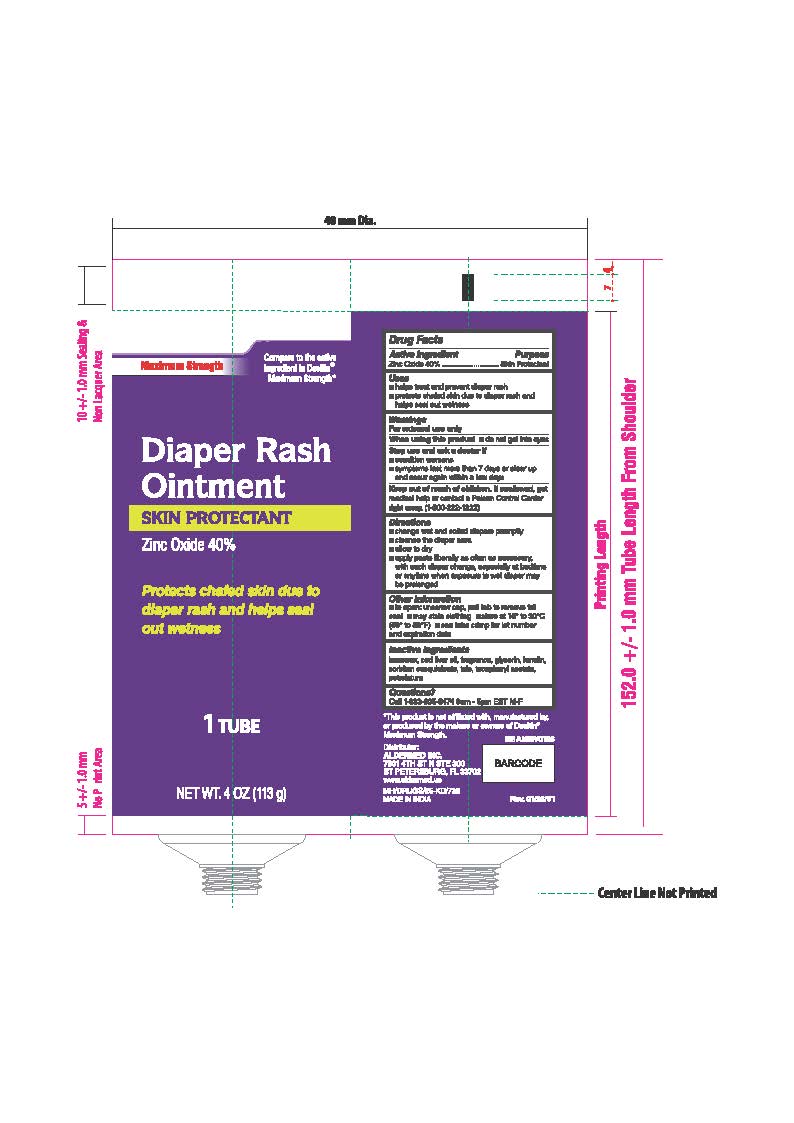 DRUG LABEL: Diaper Rash
NDC: 87236-018 | Form: OINTMENT
Manufacturer: Aldermed Inc.
Category: otc | Type: HUMAN OTC DRUG LABEL
Date: 20260212

ACTIVE INGREDIENTS: ZINC OXIDE 40 g/100 g
INACTIVE INGREDIENTS: .ALPHA.-TOCOPHEROL ACETATE; TALC; PETROLATUM; BEESWAX; COD LIVER OIL; GLYCERIN; LANOLIN; SORBITAN SESQUIOLEATE

Diaper Rash Ointment

Active ingredient

Zinc Oxide 40%

Purpose

Skin Protectant

Uses

■ helps treat and prevent diaper rash

■ protects chafed skin due to diaper rash and helps seal out wetness

Warnings

For External Use Only

When using this product

do not get into eyes

Stop use and ask a doctor if

- Conditions worsens
- Symptoms last more than 7 days or clear up and occur again within a few days

Keep out of reach of children

If swallowed, get medical help or contact a Poison Control Center right away (1-800-222-1222).

Directions

■ change wet and soiled diapers promptly

■ cleanse the diaper area
■ allow to dry
■ apply paste liberally as often as necessary, with each diaper change, especially at bedtime or anytime when exposure to wet diaper may be prolonged

Other information

■ to open: unscrew cap, pull tab to remove foil seal

■ may stain clothing

■ store at 15° to 30°C (59° to 86°F)

■ see tube crimp for lot number and expiration date

Inactive Ingredients

beeswax, cod liver, fragrance, glycerin, lanolin, sorbitan sesquileate, talc, tocopheryl acetate, petrolatum

Questions?

Call 1-833-605-84-74 9am-5 pm EST M-F